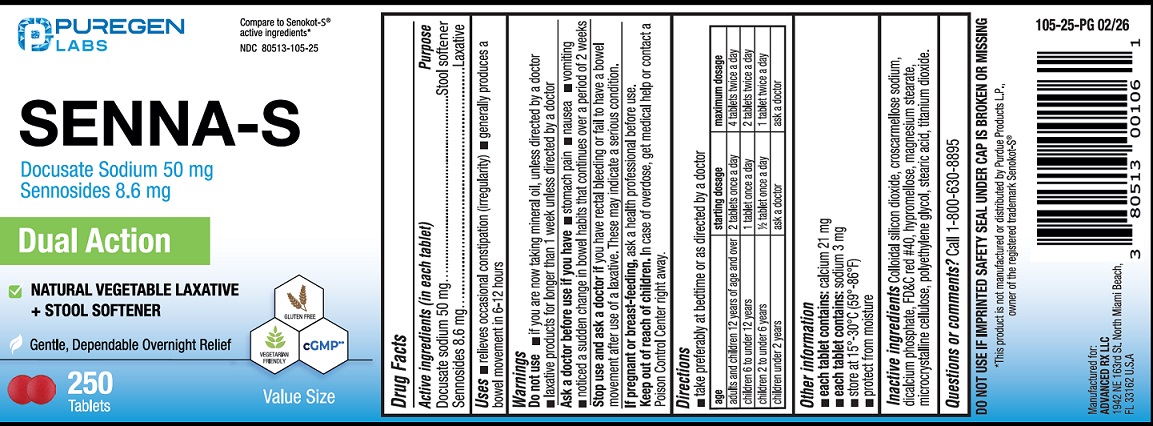 DRUG LABEL: SENNA-S
NDC: 80513-105 | Form: TABLET
Manufacturer: Advanced Rx LLC
Category: otc | Type: HUMAN OTC DRUG LABEL
Date: 20260218

ACTIVE INGREDIENTS: SENNOSIDES 8.6 mg/1 1; DOCUSATE SODIUM 50 mg/1 1
INACTIVE INGREDIENTS: CROSCARMELLOSE SODIUM; SILICON DIOXIDE; ANHYDROUS DIBASIC CALCIUM PHOSPHATE; FD&C RED NO. 40; HYPROMELLOSES; CELLULOSE, MICROCRYSTALLINE; MAGNESIUM STEARATE; POLYETHYLENE GLYCOL, UNSPECIFIED; STEARIC ACID; TITANIUM DIOXIDE

Drug Facts

ACTIVE INGREDIENT

Active ingredients (in each tablet) Purpose

Docusate sodium 50 mg.......................................Stool softner

Sennosides 8.6 mg................................................Laxative

Uses

- relieves occasional constipation (irregularity)
- generally produces a bowel movement in 6-12 hours

Warnings

Do not use

- if you are now taking mineral oil, unless directed by a doctor
- laxative products for longer than 1 week unless directed by a doctor

Ask a doctor before use if you have

- stomach pain
- nausea
- vomiting
- noticed a sudden change in bowel habits that continues over a period of 2 weeks.

Stop use and ask a doctor if

you have rectal bleeding or fail to have a bowel movement after use of a laxative. These may indicate a serious condition.

PREGNANCY OR BREAST FEEDING

If pregnant or breast-feeding, ask a health professional before use.

Keep out of reach of children.

In case of overdose, get medical help or contact a Poison Control Center right away.

Directions

take preferably at bedtime or as directed by a doctor

age | starting dosage | maximum dosage
adults and children 12 years of age and over | 2 tablets once a day | 4 tablets twice a day
children 6 to under 12 years | 1 tablet once a day | 2 tablets twice a day
children 2 to under 6 years | ½ tablet once a day | 1 tablet twice a day
children under 2 years | ask a doctor | ask a doctor

Other information

- each tablet contains:calcium 21 mg,
- each tablet contains: sodium 3 mg.
- store at 15°-30°C (59°-86°F)
- protect from moisture
- DO NOT USE IF IMPRINTED SAFETY SEAL UNDER CAP IS BROKEN OR MISSING

Inactive ingredients

Colloidal silicon dioxide, croscarmellose sodium, dicalcium phosphate, FD&C red#40, hypromellose, magnesium stearate, microcrystalline cellulose, polyethylene glycol, stearic acid, titanium dioxide.

Questions or comments?

Call 1-800-630-8895

Manufactured for:

ADVANCED RX LLC

1942 NE 163rd St.North Miami Beach,

FL 33162 U.S.A.

PRINCIPAL DISPLAY PANEL

NDC 80513-105-25

Compare to Senokot-S® active ingredients*

SENNA-S

Docusate Sodium 50 mg

Sennosides 8.6 mg

Dual Action

Natural Vegetable Laxative + Stool Softener

250 Tablets

*This product is not manufactured or distributed by Purdue Products L.P., owner of the registered trademark Senokot-S®.